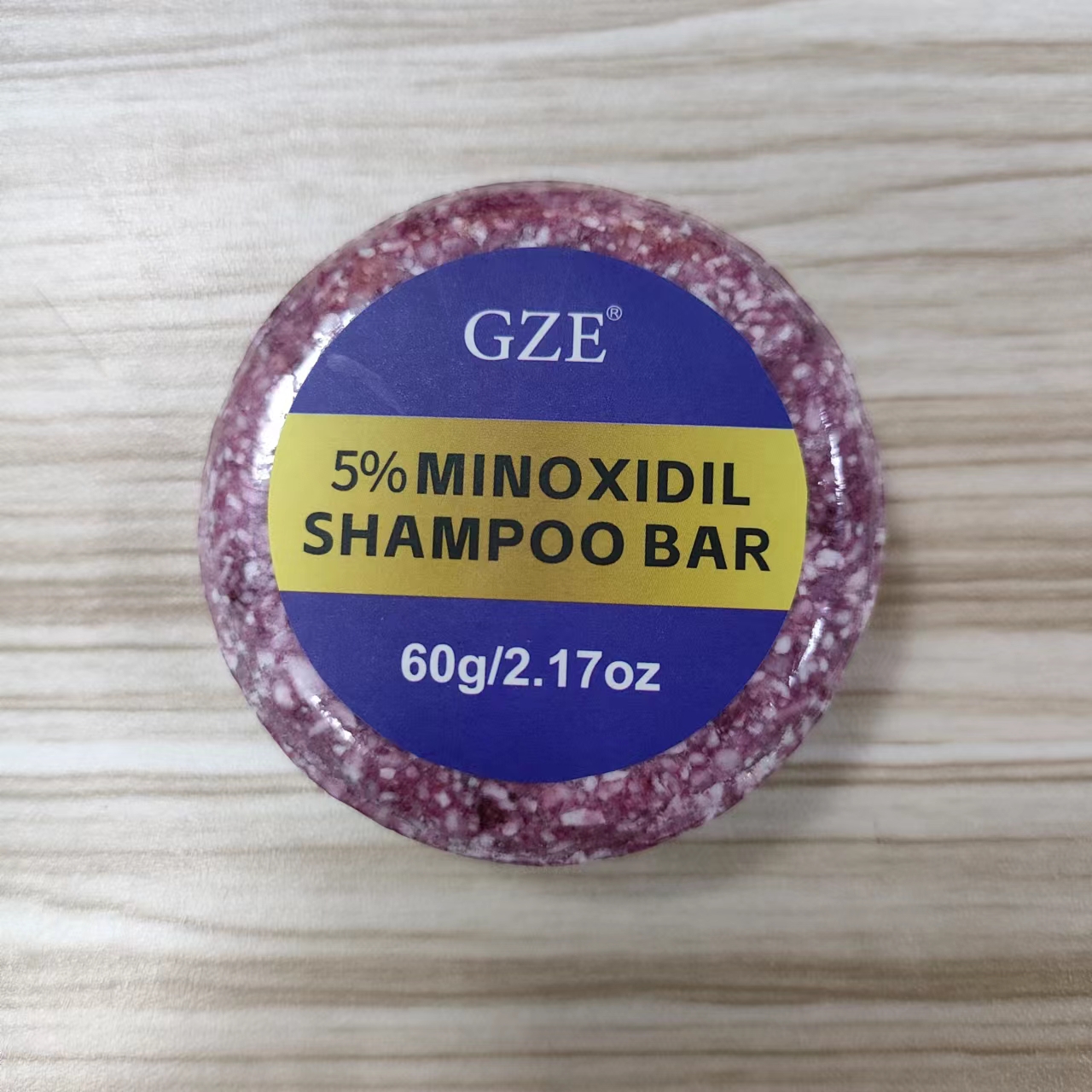 DRUG LABEL: GZE 5% Minoxidil ShampooBar
NDC: 74458-269 | Form: SOAP
Manufacturer: Guangzhou Yilong Cosmetics Co., Ltd
Category: otc | Type: HUMAN OTC DRUG LABEL
Date: 20241010

ACTIVE INGREDIENTS: MINOXIDIL 5 g/100 g
INACTIVE INGREDIENTS: GLYCERIN; HYDROGENATED CASTOR OIL

GZE 5% MINOXIDIL SHAMPOO BAR

ACTIVE INGREDIENT

Minoxidil.

INACTIVE INGREDIENT

Glycerin, Hydrogenated Castor Oil

PURPOSE

Anti-dandruff and anti-hair loss.

INDICATIONS AND USAGE

After you’ve wet your hair, take shampoo bar and either rub the bar between your hands and massage the lather into your hair. Rinse as you’d normally do and repeat as desired.

WARNINGS

For external use only.

Do not use on damaged or broken skin.

When using this product keep out of eyes. Rinse with water to remove.

Keep out of reach of children. If swallowed, get medical help or contact a Poison Control Center right away.

DOSAGE AND ADMINISTRATION

After you’ve wet your hair, take shampoo bar and either rub the bar between your hands and massage the lather into your hair. Rinse as you’d normally do and repeat as desired.